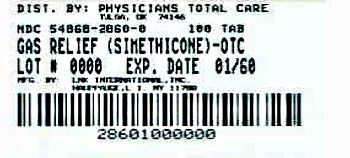 DRUG LABEL: Gas Relief
NDC: 54868-2860 | Form: TABLET, CHEWABLE
Manufacturer: Physicians Total Care, Inc.
Category: otc | Type: HUMAN OTC DRUG LABEL
Date: 20120502

ACTIVE INGREDIENTS: DIMETHICONE 80 mg/1 1
INACTIVE INGREDIENTS: DEXTROSE; SILICON DIOXIDE; TALC

Leader 44-137

Active ingredients

Simethicone 80 mg

Purpose

Antigas

Use(s)

relieves these symptoms associated with gas

- bloating
- pressure
- stuffed feeling
- fullness

Warnings

If pregnant or breast-feeding,

ask a health professional before use.

Directions

- do not exceed 6 tablets per day unless directed by a doctor
- chew 1 to 2 tablets thoroughly as needed after meals and at bedtime

Other information

- store at room temperature
- avoid high humidity and excessive heat, above 40ºC (104ºF)

Inactive ingredients

dextrose, peppermint flavor, silica gel, sorbitol, stearic acid, talc, tri-calcium phosphate

Principal display panel

NDC 54868-2860-0

Simethicone 80 mg

Gas Relief

•Pressure •Bloating •Discomfort

Fast Acting

Anti Gas

Mind Flavored

100 Tablets

TAMPER EVIDENT: DO NOT USE IF IMPRINTED SAFETY SEAL UNDER CAP IS BROKEN OR MISSING

50844 REV1104E13712

DISTRIBUTED BY CARDINAL HEALTH, DUBLIN, OHIO 43017

Additional barcode labeling by:
Physicians Total Care, Inc.
Tulsa, Oklahoma 74146